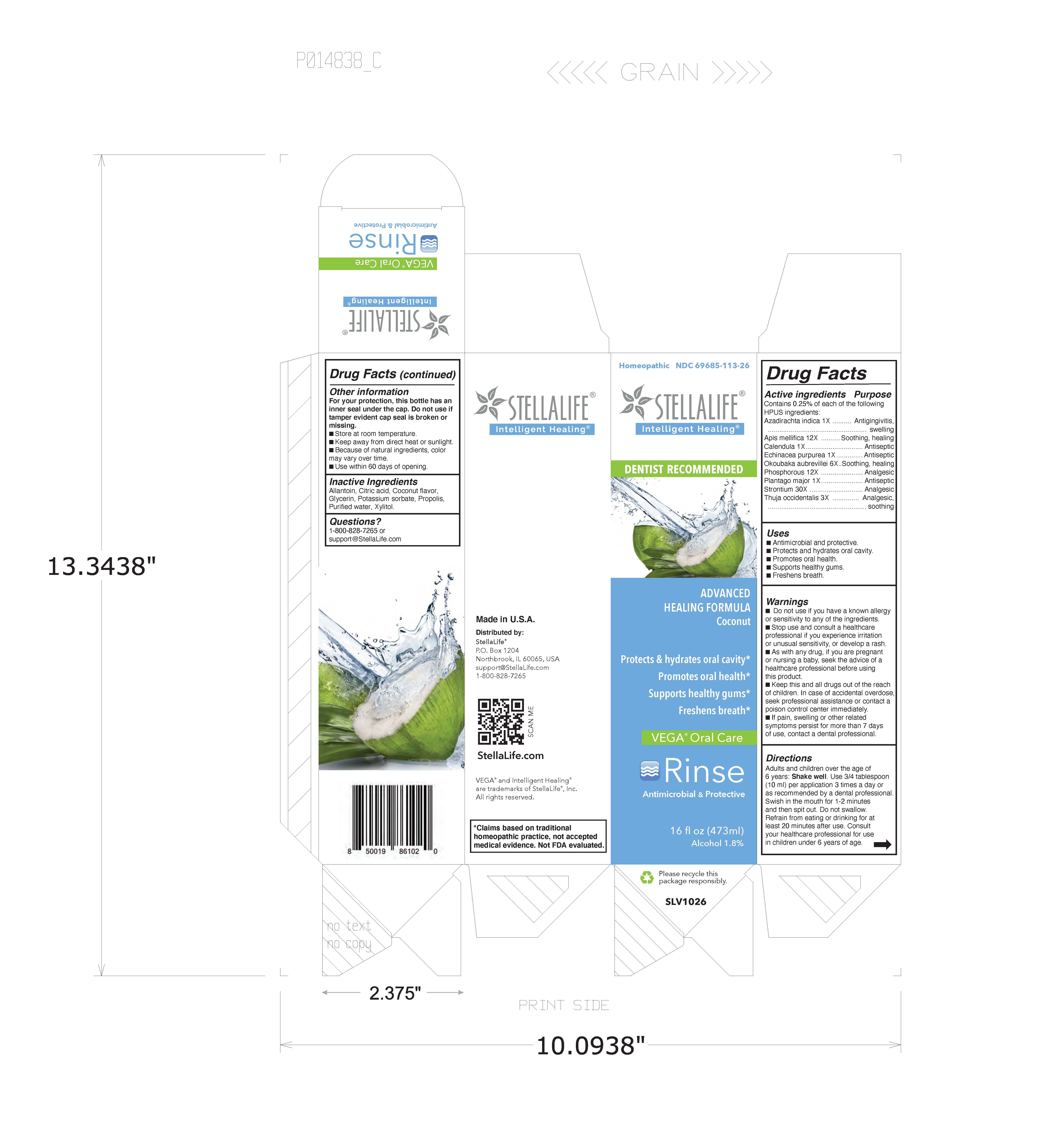 DRUG LABEL: StellaLife VEGA Oral Care Coconut
NDC: 61727-119 | Form: RINSE
Manufacturer: Homeocare Laboratories, Inc.
Category: homeopathic | Type: HUMAN OTC DRUG LABEL
Date: 20251224

ACTIVE INGREDIENTS: CALENDULA OFFICINALIS FLOWER 1 [hp_X]/1 mL; APIS MELLIFERA 12 [hp_X]/1 mL; PLANTAGO MAJOR 1 [hp_X]/1 mL; AZADIRACHTA INDICA BARK 1 [hp_X]/1 mL; THUJA OCCIDENTALIS LEAFY TWIG 3 [hp_X]/1 mL; ECHINACEA PURPUREA 1 [hp_X]/1 mL; STRONTIUM 30 [hp_X]/1 mL; OKOUBAKA AUBREVILLEI BARK 6 [hp_X]/1 mL; PHOSPHORUS 12 [hp_X]/1 mL
INACTIVE INGREDIENTS: XYLITOL; PROPOLIS WAX; POTASSIUM SORBATE; COCONUT; CITRIC ACID MONOHYDRATE; GLYCERIN; ALLANTOIN; WATER

StellaLife VEGA Oral Care Coconut Rinse

Drug Facts

Contains 0.25% of each of the following HPUS ingredients:

Active Ingredients | Purpose
Azadirachta indica 1X | Antigingivitis, swelling
Apis mellifica 12X | Soothing, healing
Calendula 1X | Antiseptic
Echinacea purpurea 1X | Antiseptic
Okoubaka aubrevellei 6X | Soothing, healing
Phosphorous 12X | Anaglesic
Plantago major 1X | Antiseptic
Strontium 30X | Analgesic
Thuja occidentalis 3X | Analgesic, soothing

Uses

Promotes oral health

Hydrates oral cavity

Supports healthy gums

Freshens breath

Usage

- Antimicrobial
- Promotes oral health
- Hydrates oral cavity
- Supports healthy gums
- Freshens breath.

Warnings

- Do not use if you have a known allergy or sensitivity to any of the following ingredients
- Stop use and consult a healthcare professional if you experience irritation or unusual sensitivity, or develop a rash.
- As with any drug, if you are pregnant or nursing a baby, seek the advise of a healthcare professional before using this product.
- Keep this and all drugs out of the reach of children. In case of accidental overdose, seek professional assistance or contact poison control center immediately.
- If pain, swelling or other related symptoms persist for more than 7 days of use, contact a dental professional.

Keep Out of Reach of Children

Keep this and all drugs out of reach of children. In case of accidental overdose, seek professional assistance or contact a poison control center immediately.

Directions

Adults and children ovver the age of 6 years: Shake well. Use 3/4 tablespoon (10 ml) per application 3 times a day. Swish in the mouth for 1-2 minutes abnd then spit out. Do not swallow. Refrain from eating or drinking for at least 20 minutes after use. Consult your healthcare professional for use in children under 6 years of age.

Other Information

For your protection, this bottle has a full body seal. Do not use if this tamper evident seal is broken or missing.

- Store at toom temperature.
- Keep away from direct heat or sunlight.
- Because of natural ingredients, color may vary over time.
- Use within 60 days of opening.

Inactive Ingredients

ALLANTOIN, WATER, XYLITOL, POTASSIUM SORBATE, COCONUT, CITRIC ACID MONOHYDRATE, GLYCERIN